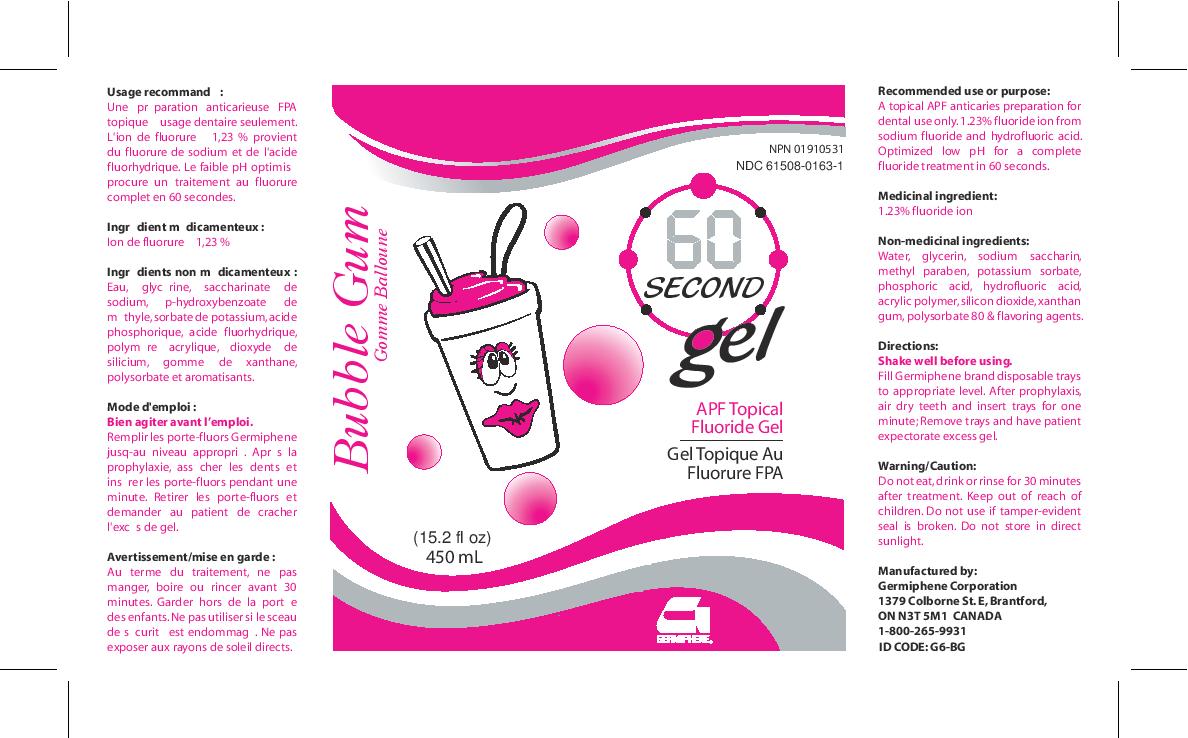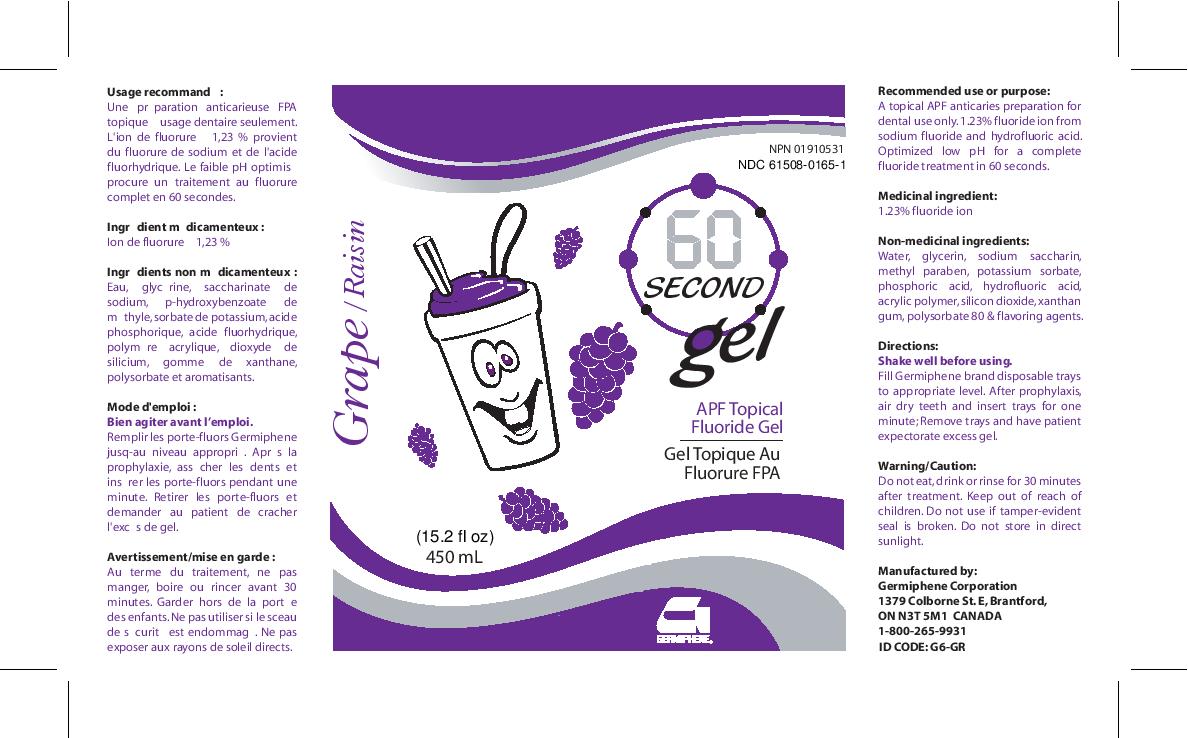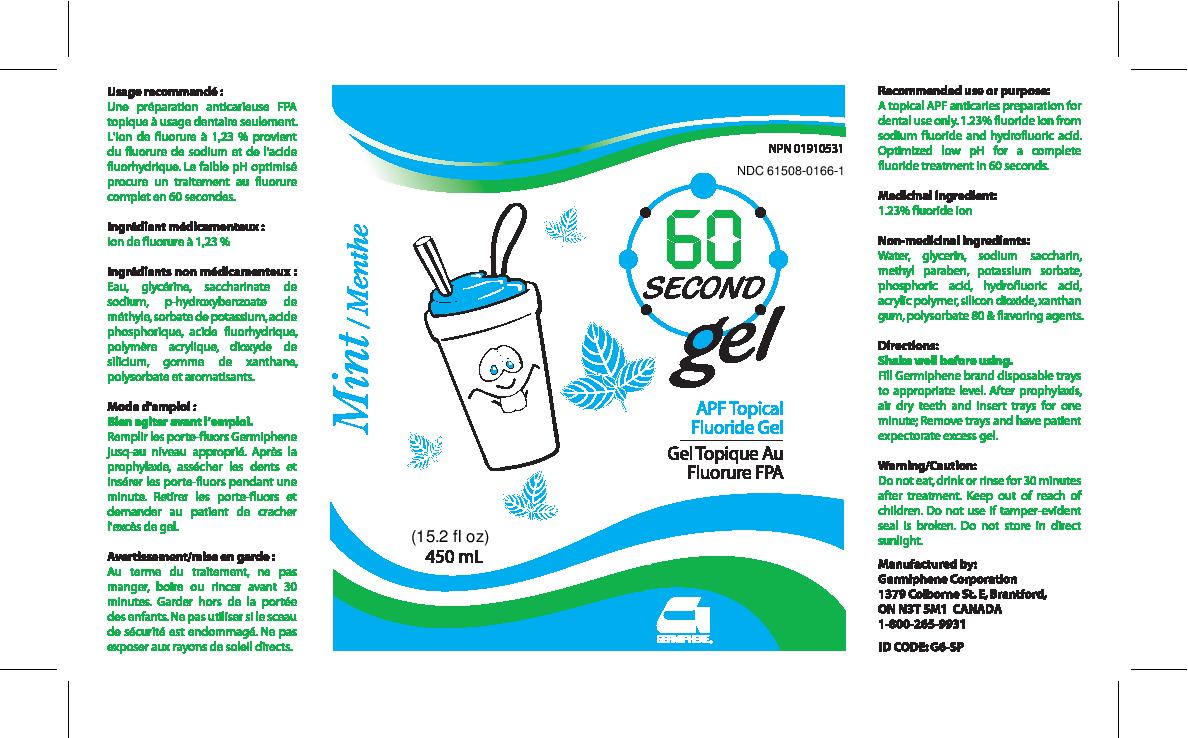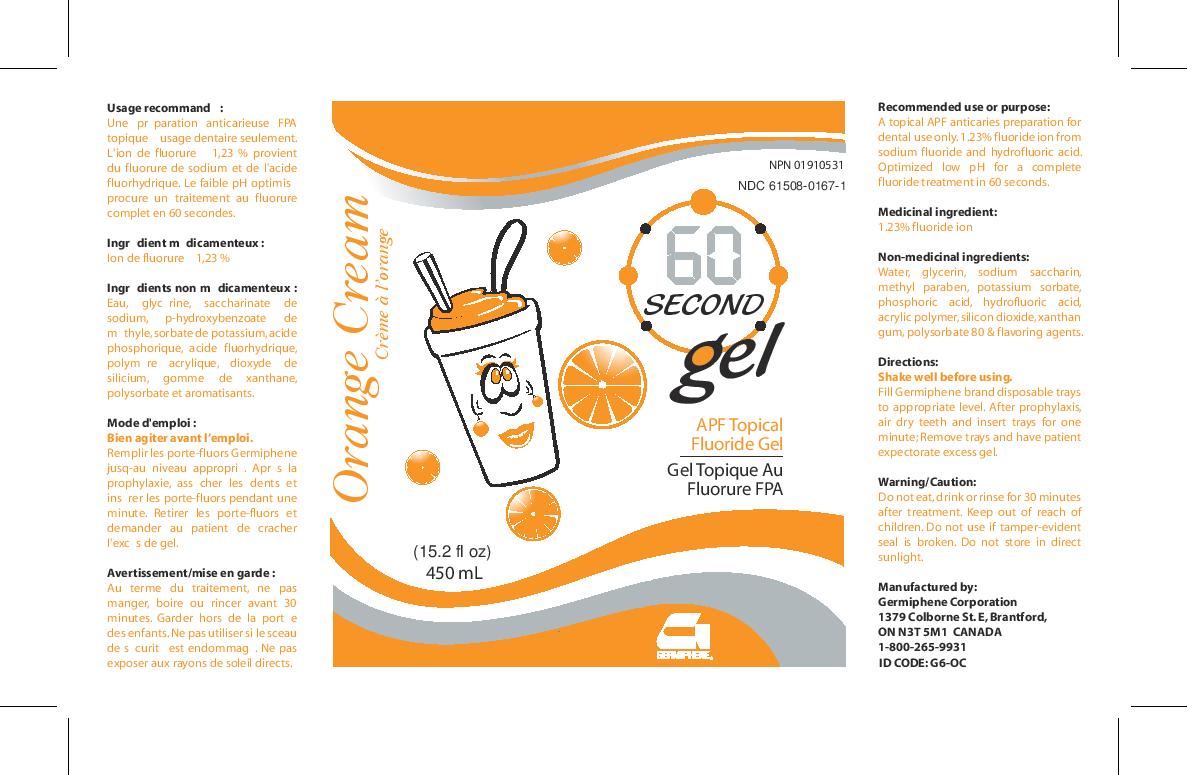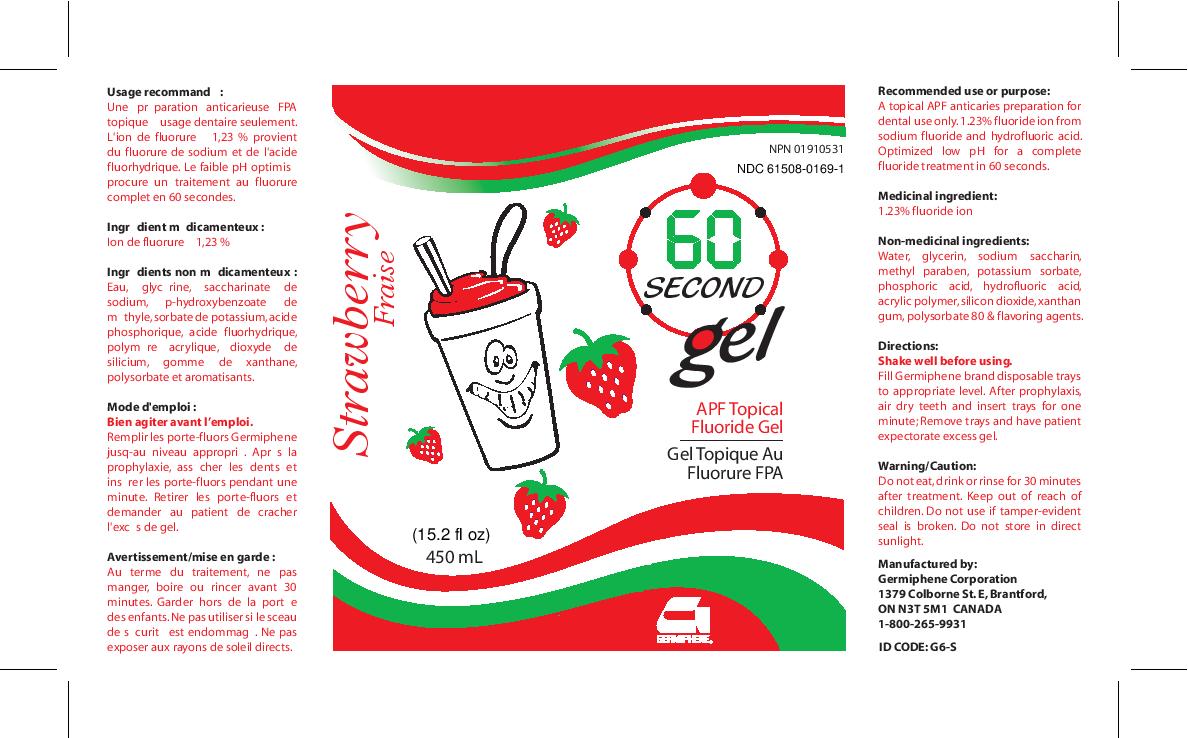 DRUG LABEL: 60 Second Gel Bubblegum
NDC: 61508-0163 | Form: GEL, DENTIFRICE
Manufacturer: Germiphene Corporation
Category: otc | Type: HUMAN OTC DRUG LABEL
Date: 20170214

ACTIVE INGREDIENTS: SODIUM FLUORIDE 1.69 g/100 g
INACTIVE INGREDIENTS: SILICON DIOXIDE 0.55 g/100 g; METHYLPARABEN 0.08 g/100 g; WATER 84.365 g/100 g; PHOSPHORIC ACID 0.933 g/100 g; GLYCERIN 7 g/100 g; POTASSIUM SORBATE 0.1 g/100 g; HYDROFLUORIC ACID 1 g/100 g; CARBOXYPOLYMETHYLENE 1 g/100 g; SACCHARIN SODIUM 0.2 g/100 g; XANTHAN GUM 1 g/100 g; POLYSORBATE 80 0.1 g/100 g

60 Second Gel

Recommended use or purpose:

A topical APF anticaries preparation for dental use only.

PURPOSE

1.23% fluoride ion from sodium fluoride and hydrofluoric acid. Optimized low pH for a complete fluoride treatment in 60 seconds.

Medicinal Ingredient:

1.23% fluoride ion

Non-medicinal ingredients:

Water, glycerin, sodium saccharin, methyl paraben, potassium sorbate, phosphoric acid, hydrofluoric acid, acrylic polymer, silicon dioxide, zanthan gum, polysorbate 80 & flavoring agents.

Directions:

Shake well before using. Fill Germiphene brand disposable trays to appropriate level. After prophylaxis, air dry teeth and insert trays for one minute. Remove trays and have patient expectorate excess gel.

Keep out of reach of children.

Warning/Caution:

Do not eat, drink, or rinse for 30 minutes after treatment. Do not use if tamper-evident seal is broken. Do not store in direct sunlight.